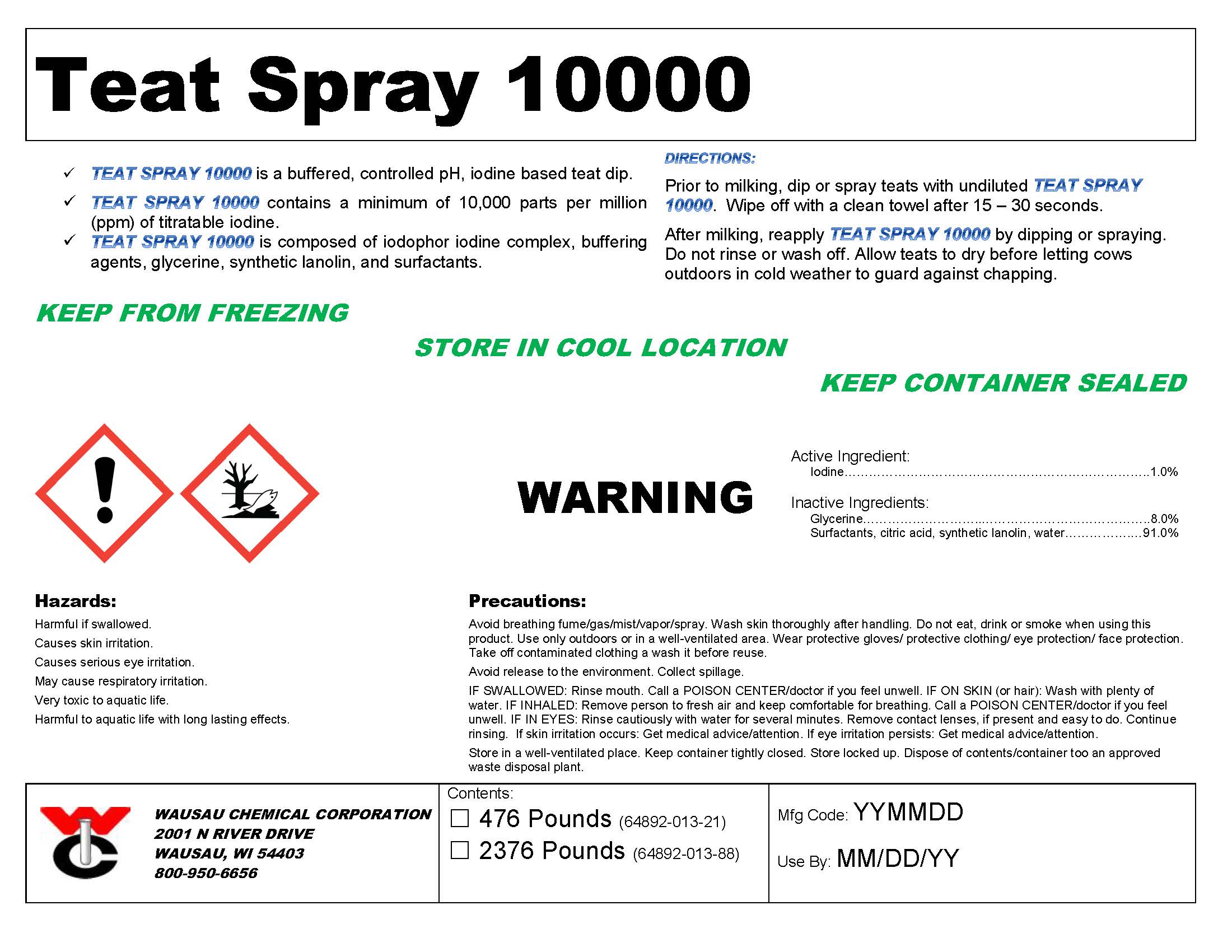 DRUG LABEL: Teat-Spray 10000
NDC: 64892-013 | Form: SPRAY
Manufacturer: Wausau Chemical
Category: animal | Type: OTC ANIMAL DRUG LABEL
Date: 20180315

ACTIVE INGREDIENTS: IODINE 10000 mg/1 L

DISPOSAL AND WASTE HANDLING

Dispose of contents/container to an approved waste disposal plant.

ENVIRONMENTAL WARNING

Very toxic to aquatic life. Harmful to aquatic life with long lasting effects.

Avoid release to the environment. Collect spillage.

GENERAL PRECAUTIONS

WARNING / Keep from freezing / Store in cool location / Keep container sealed

First Aid:

IF SWALLOWED: Rinse mouth. Call a POISON CENTER/doctor if you feel unwell.

IF ON SKIN (or hair): Wash with plenty of water.

IF INHALED: Remove person to fresh air and keep comfortable for breathing. Call a POISON CENTER/doctor if you feel unwell.

IF IN EYES: Rinse cautiously with water for several minutes. Remove contact lenses, if present and easy to do. Continue rinsing.

If skin irritation occurs: Get medical advice/attention.

If eye irritation persists: Get medical advice/attention.

SAFE HANDLING WARNING

Harmful if swallowed.
Causes skin irritation.
Causes serious eye irritation.
May cause respiratory irritation.

Avoid breathing fume/gas/mist/vapor/spray.Wash skin thoroughly after handling. Do not eat, drink or smoke when using this product. Use only outdoors or in a well-ventilated area. Wear protective gloves/ protective clothing/ eye protection/ face protection. Take off contaminated clothing a wash it before reuse.

STORAGE AND HANDLING

Store in a well-ventilated place.

Keep container tightly closed.

Store locked up.

DIRECTIONS:
Prior to milking, dip or spray teats with undiluted TEAT SPRAY 10000. Wipe off with a clean towel after 15 – 30 seconds.

After milking, reapply TEAT SPRAY 10000 by dipping or spraying. Do not rinse or wash off. Allow teats to dry before letting cows outdoors in cold weather to guard against chapping.

Active Ingredient:
Iodine.....................................................................................1.0%

Inactive Ingredients:
Glycerine.................................................................................8.0%
Surfactants, citric acid, synthetic lanolin, water.....................91.0%

Wausau Chemical Corporation

2001 N River Drive

Wausau, WI 54403

800-950-6656